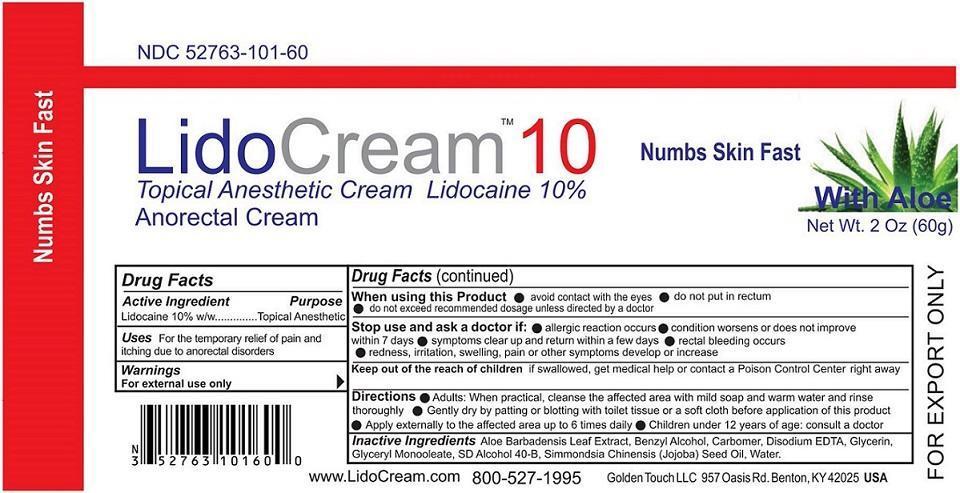 DRUG LABEL: LidoCream 10
NDC: 52763-101 | Form: CREAM
Manufacturer: Golden Touch LLC
Category: otc | Type: HUMAN OTC DRUG LABEL
Date: 20151111

ACTIVE INGREDIENTS: LIDOCAINE 10 g/100 g
INACTIVE INGREDIENTS: ALOE VERA LEAF; BENZYL ALCOHOL; CARBOMER HOMOPOLYMER TYPE C (ALLYL PENTAERYTHRITOL CROSSLINKED); EDETATE DISODIUM; GLYCERIN; GLYCERYL OLEATE; ALCOHOL; SIMMONDSIA CHINENSIS SEED; WATER

LidoCream 10

Active Ingredient

Lidocaine 10% w/w

Purpose

Topical Anesthetic

Keep out of reach of children if swallowed, get medical help or contact a Poison Control Center right away.

INDICATIONS AND USAGE

Uses For the temporary relief of pain and itching due to anorectal disorders

Warnings

For external use only

When using this product • avoid contact with eyes • do not put in rectum • do not exceed recommended dosage unless directed by a doctor

Stop use and ask a doctor if: • allergic reaction occurs • condition worsens or does not improve within 7 days • symptoms clear up and return within a few days • rectal bleeding occurs • redness, irritation, swelling, pain or other symptoms develop or increase

DOSAGE AND ADMINISTRATION

Directions • Adults: When practical, cleanse the affected area with mild soap and warm water and rinse thoroughly • Gently dry by patting or blotting with toilet tissue or a soft cloth before application of this product • Apply externally to the affected area upto 6 times daily • Children under 12 years of age: consult a doctor

INACTIVE INGREDIENT

Inactive Ingredients Aloe Barbadensis Leaf Extract, Benzyl Alcohol, Carbomer, Disodium EDTA, Glycerin, Glyceryl Monooleate, SD Alcohol 40-B, Simmondsia Chinensis (Jojoba) Seed Oil, Water.